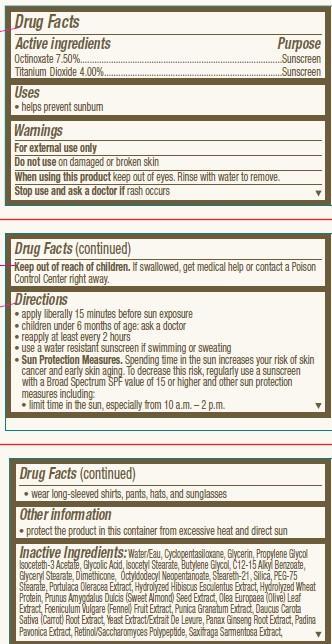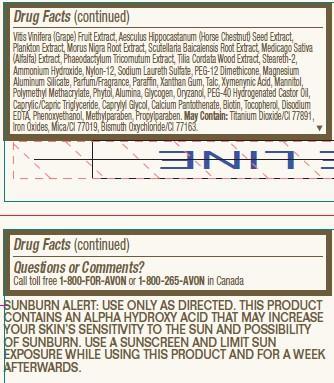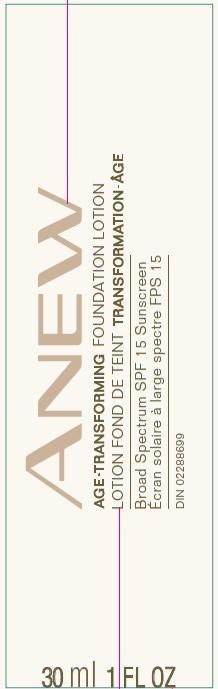 DRUG LABEL: Anew Age-Transforming
NDC: 10096-0171 | Form: LOTION
Manufacturer: Avon Products, Inc
Category: otc | Type: HUMAN OTC DRUG LABEL
Date: 20130210

ACTIVE INGREDIENTS: OCTINOXATE 75 mg/1 mL; TITANIUM DIOXIDE 40 mg/1 mL

Active ingredients
Octinoxate 7.50%.........................................................................
Titanium Dioxide 4.00%.................................................................

Purpose
..............................Sunscreen
...........................Sunscreen

Uses
• helps prevent sunburn

Warnings
For external use only

Do not use on damaged or broken skin

When using this product keep out of eyes. Rinse with water to remove.

Stop use and ask a doctor if rash occurs

Keep out of reach of children. If swallowed, get medical help or contact a Poison Control Center right away.

Directions
• apply liberally 15 minutes before sun exposure
• children under 6 months of age: ask a doctor
• reapply at least every 2 hours
• use a water resistant sunscreen if swimming or sweating
• Sun Protection Measures. Spending time in the sun increases your risk of skin
cancer and early skin aging. To decrease this risk, regularly use a sunscreen
with a Broad Spectrum SPF value of 15 or higher and other sun protection
measures including:
• limit time in the sun, especially from 10 a.m. – 2 p.m.

• wear long-sleeved shirts, pants, hats, and sunglasses

Other information
• protect the product in this container from excessive heat and direct sun

INACTIVE INGREDIENT

Inactive Ingredients:Water/Eau, Cyclopentasiloxane, Glycerin, Propylene Glycol Isoceteth-3 Acetate, Glycolic Acid, Isocetyl Stearate, Butylene Glycol, C12-15 Alkyl Benzoate, Glyceryl Stearate, Dimethicone, Octyldodecyl Neopentanoate, Steareth-21, Silica, PEG-75 Stearate, Portulaca Oleracea Extract, Hydrolyzed Hibiscus Esculentus Extract, Hydrolyzed Wheat Protein, Prunus Amygdalus Dulcis (Sweet Almond) Seed Extract, Olea Europaea (Olive) Leaf Extract, Foeniculum Vulgare (Fennel) Fruit Extract, Punica Granatum Extract, Daucus Carota Sativa (Carrot) Root Extract, Yeast Extract/Extrait De Levure, Panax Ginseng Root Extract, Padina Pavonica Extract, Retinol/Saccharomyces Polypeptide, Saxifraga Sarmentosa Extract, Vitis Vinifera (Grape) Fruit Extract, Aesculus Hippocastanum (Horse Chestnut) Seed Extract, Plankton Extract, Morus Nigra Root Extract, Scutellaria Baicalensis Root Extract, Medicago Sativa (Alfalfa) Extract, Phaeodactylum Tricornutum Extract, Tilia Cordata Wood Extract, Steareth-2, Ammonium Hydroxide, Nylon-12, Sodium Laureth Sulfate, PEG-12 Dimethicone, Magnesium Aluminum Silicate, Parfum/Fragrance, Paraffin, Xanthan Gum, Talc, Xymenynic Acid, Mannitol, Polymethyl Methacrylate, Phytol, Alumina, Glycogen, Oryzanol, PEG-40 Hydrogenated Castor Oil, Caprylic/Capric Triglyceride, Caprylyl Glycol, Calcium Pantothenate, Biotin, Tocopherol, Disodium EDTA, Phenoxyethanol, Methylparaben, Propylparaben. May Contain: Titanium Dioxide/CI 77891, Iron Oxides, Mica/CI 77019, Bismuth Oxychloride/CI 77163.

Questions or Comments?
Call toll free 1-800-FOR-AVON or 1-800-265-AVON in Canada